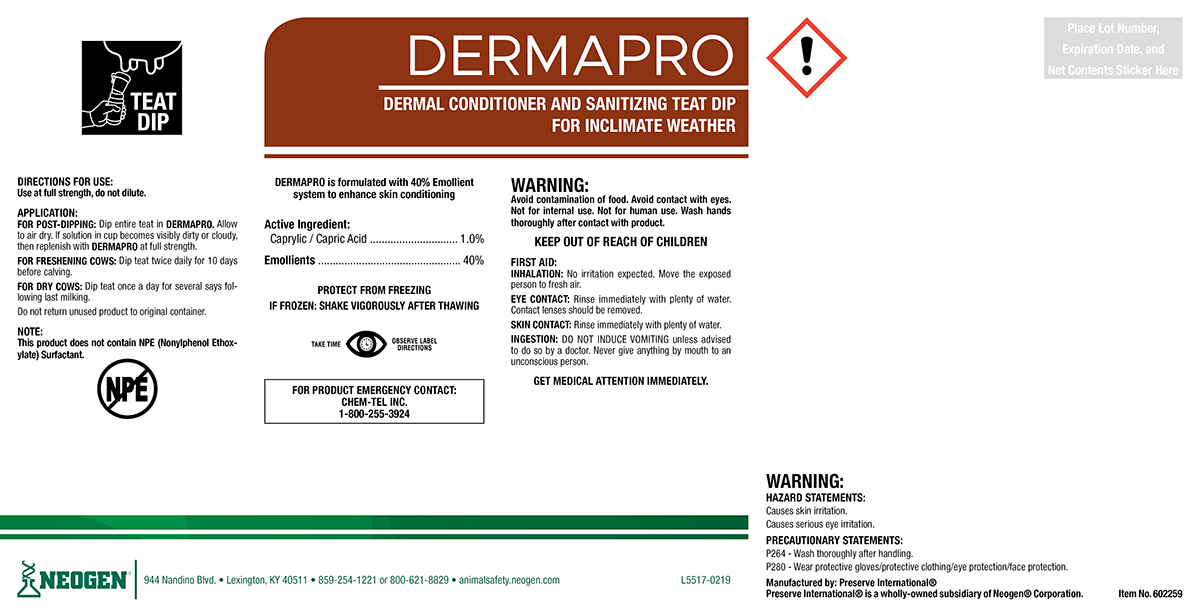 DRUG LABEL: Dermapro
NDC: 60648-9017 | Form: SOLUTION
Manufacturer: Preserve International
Category: animal | Type: OTC ANIMAL DRUG LABEL
Date: 20190521

ACTIVE INGREDIENTS: CAPRYLIC/CAPRIC ACID 11.15 g/1 L

DERMAPRO

DIRECTIONS FOR USE:

Use at full strength, do not dilute.

APPLICATION:

FOR POST-DIPPING: Dip entire teat in DERMAPRO. Allow to air dry. If solution in cup becomes visibly dirty or cloudy, then replenish with DERMAPRO at full strength.

FOR FRESHENING COWS: Dip teat twice daily for 10 days before calving.

FOR DRY COWS: Dip teat once a day for several days following last milking.

Do not return unused product to original container.

NOTE:

This product does not contain NPE (Nonylphenol Ethoxylate) Surfactant.

WARNINGS AND PRECAUTIONS

PROTECT FROM FREEZING

IF FROZEN: SHAKE VIGOROUSLY AFTER THAWING

WARNINGS AND PRECAUTIONS

TAKE TIME OBSERVE LABEL DIRECTIONS

WARNING:

Avoid contamination of food. Avoid contact with eyes. Not for internal use. Not for human use. Wash hands thoroughly after contact with product.

KEEP OUT OF REACH OF CHILDREN

FIRST AID:

INHALATION: No irritation expected. Move the exposed person to fresh air.

EYE CONTACT: Rinse immediately with plenty of water. Contact lenses should be removed.

SKIN CONTACT: No irritation expected. Rinse immediately with plenty of water.

INGESTION: DO NOT INDUCE VOMITING unless advised to do so by a doctor. Never give anything by mouth to an unconscious person.
GET MEDICAL ATTENTION IMMEDIATELY.

FOR PRODUCT EMERGENCY CONTACT: Chem-Tel Inc. 1-800-255-3924

WARNING:

HAZARD STATEMENTS:

Causes skin irritation.

Causes serious eye irritation.

PRECAUSTIONARY STATEMENTS:

P264 - Wash thoroughly after handling.

P280 - Wear protective gloves/protective clothing/eye protection/face protection.

PACKAGE LABEL

DERMAPRO

DERMAL CONITIONER AND SANITIZING TEAT DIP FOR INCLIMATE WEATHER

DERMAPRO is formulated with 40% Emollient system to enhance skin conditioning

Active Ingredient:

Caprylic/Capric Acid......... 1.0%
Emollients........................ 40%

Manufactured By: Preserve International®

Preserve International® is a wholly-owned subsidiary of Neogen® Corporation.

NEOGEN®

944 Nandino Blvd.

Lexington, KY 40511

859-254-1221 or 800-621-8829

animalsafety.neogen.com